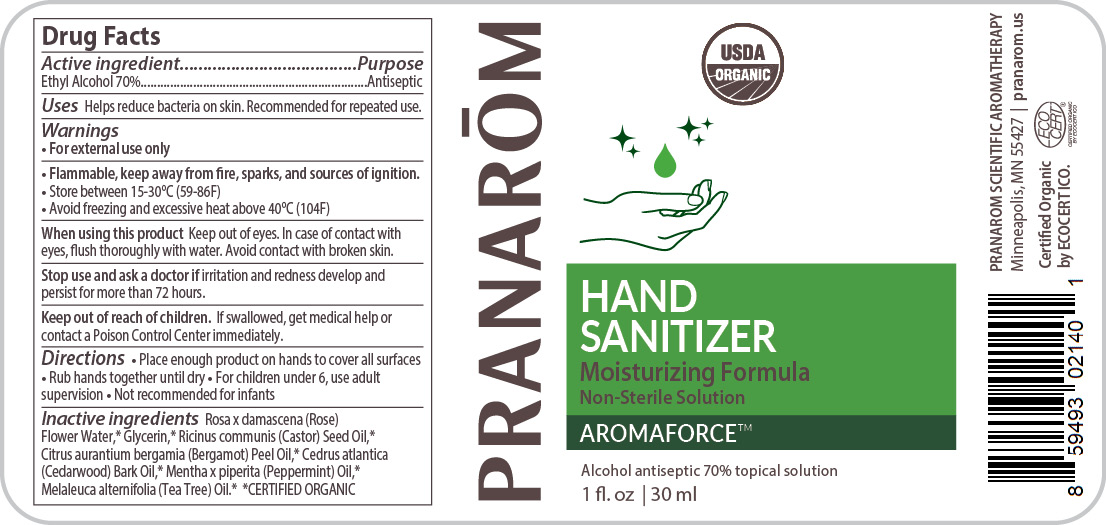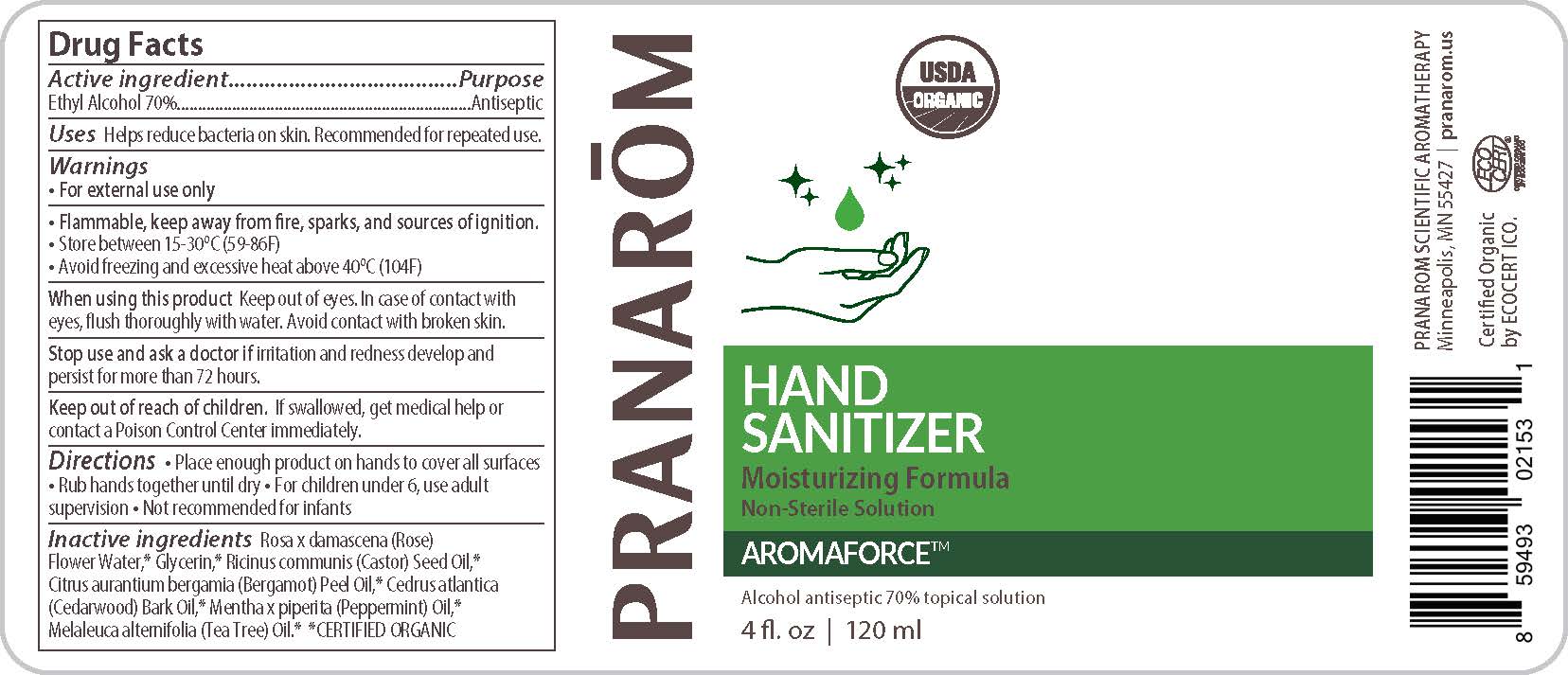 DRUG LABEL: Pranarom Aromaforce Alcohol antiseptic
NDC: 78596-001 | Form: LIQUID
Manufacturer: Veriditas Botanicals LLC
Category: otc | Type: HUMAN OTC DRUG LABEL
Date: 20200601

ACTIVE INGREDIENTS: ALCOHOL 70 mL/100 mL
INACTIVE INGREDIENTS: GLYCERIN; CASTOR OIL; PEPPERMINT OIL; CEDRUS ATLANTICA BARK OIL; TEA TREE OIL; BERGAMOT OIL; WATER; ROSA X DAMASCENA FLOWER OIL

Hand Sanitizer

Active Ingredient(s)

Ethyl Alcohol 70% v/v. Purpose: Antiseptic

Purpose

Antiseptic, Hand Sanitizer

Use

Helps reduce bacteria on skin. Recommended for repeated use.

Warnings

For external use only.

Other information

- Flammable. Keep away from fire, sparks, and sources of ignition.
- Store between 15-30C (59-86F)
- Avoid freezing and excessive heat above 40C (104F)

When using this product Keep out of eyes. In case of contact with eyes, fush thoroughly with water. Avoid contact with broken skin.

Stop use and ask a doctor if irritation and redness develop and persist for more than 72 hours.

Keep out of reach of children. If swallowed, get medical help or contact a Poison Control Center immediately.

Directions

Place enough product on hands to cover all surfaces. Rub hands together until dry. For children under 6, use adult
supervision. Not recommended for infants.

Inactive ingredients

Rosa x damascena (Rose) Flower Water,* Glycerin,* Ricinus communis (Castor) Seed Oil,* Citrus aurantium bergamia (Bergamot) Peel Oil,* Cedrus atlantica (Cedarwood) Bark Oil,* Mentha x piperita (Peppermint) Oil,* Melaleuca alternifolia (Tea Tree) Oil.* *CERTIFIED ORGANIC

Package Label - Principal Display Panel

PRANARÕM

HAND SANITIZER

Moisturizing Formula

Non-Sterile Solution

AROMAFORCE(TM)

Alcohol antiseptic 70% topical solution

xx fl. oz | xx ml

PRANAROM SCIENTIFIC AROMATHERAPY

Minneapolis, MN 55427 | pranarom.us

Certified Organic

by ECOCERT ICO.